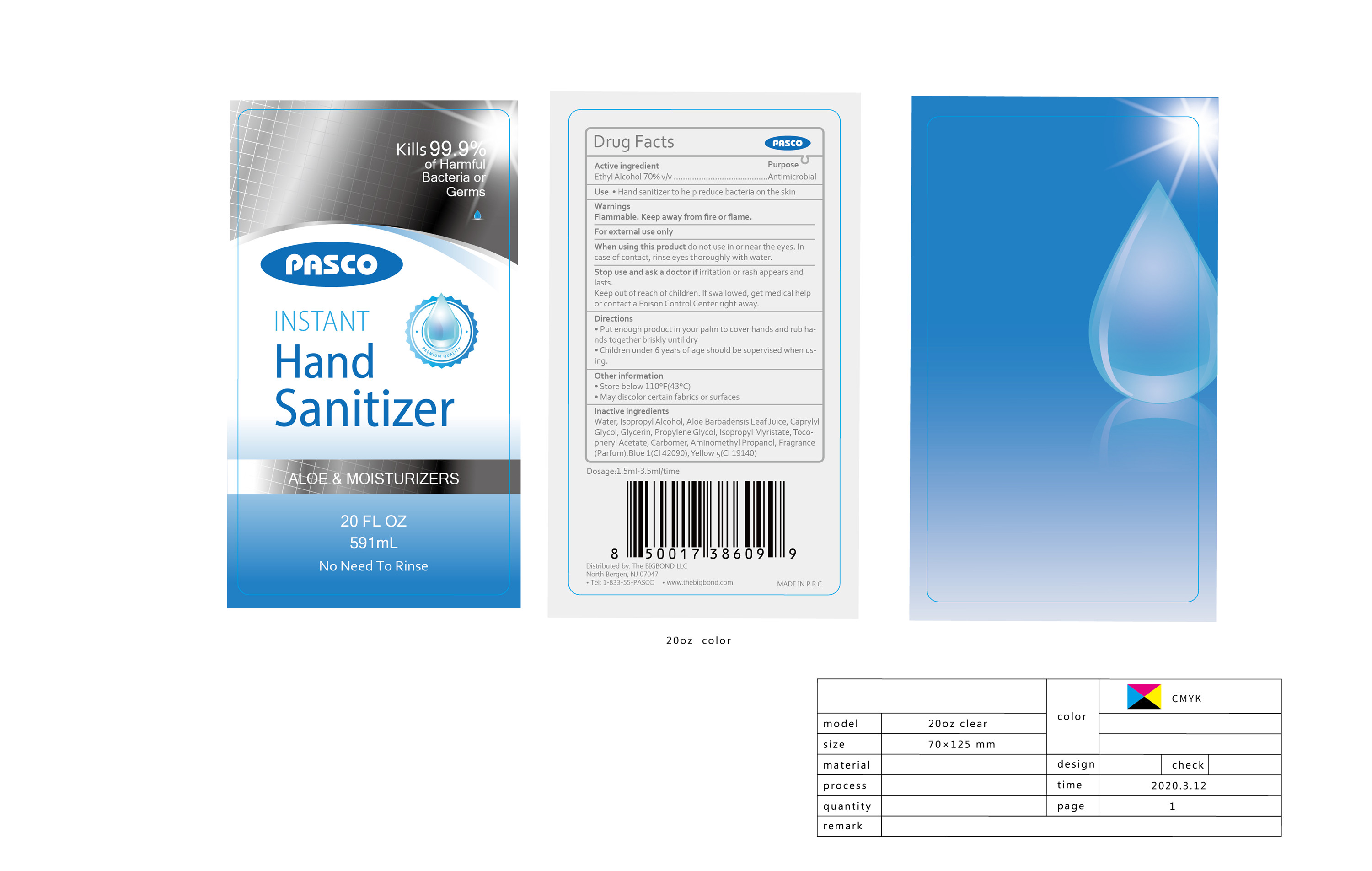 DRUG LABEL: Instant hand sanitizer
NDC: 87052-119 | Form: LIQUID
Manufacturer: THE BIGBOND LLC
Category: otc | Type: HUMAN OTC DRUG LABEL
Date: 20200507

ACTIVE INGREDIENTS: ALCOHOL 413.7 mL/591 mL
INACTIVE INGREDIENTS: ISOPROPYL MYRISTATE; FD&C BLUE NO. 1; FD&C YELLOW NO. 5; PROPYLENE GLYCOL; ISOPROPYL ALCOHOL; .ALPHA.-TOCOPHEROL ACETATE; CARBOMER HOMOPOLYMER, UNSPECIFIED TYPE; ALOE VERA LEAF; CAPRYLYL GLYCOL; GLYCERIN; AMINOMETHYLPROPANOL; WATER

DOSAGE AND ADMINISTRATION

1.5m1-3 5ml/time; Store below 110°F (43°C) ; May discolor certain fabrics of surfaces

keep out of reach of children

INDICATIONS AND USAGE

Take appropriate amount of this product to moisten your hands and rub for one minute until the liquid covers the whole surface

keep out of reach of children

PURPOSE

Disinfection
Sterilization
No Rinseing

ACTIVE INGREDIENT

Ethyl alcohol